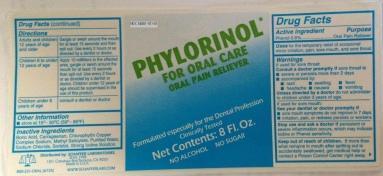 DRUG LABEL: Phylorinol
NDC: 54061-101 | Form: LIQUID
Manufacturer: Schaffer Laboratories
Category: otc | Type: HUMAN OTC DRUG LABEL
Date: 20140325

ACTIVE INGREDIENTS: PHENOL .25 mg/100 mL
INACTIVE INGREDIENTS: WATER

OTC - ACTIVE INGREDIENT SECTION

Drug Facts

Active Ingredient

Phenol 0.6%...............Oral Pain Reliever

Uses

- temporary relief of occasional minor irritation, pain, sore mouth, and sore throat.

Warnings

If used for sore throat:

Consult a doctor promplty if sore throat is

- severe or persists more than 2 days
- accompanied by :
- rash
- swelling
- fever
- headache
- nausea
- vomiting

Unless directed by a doctor do not administer to children under 3 years of age.

If used for sore mouth:

See your dentist or doctor promptly if

- sore mouth symptoms do not improve in 7 days.
- irritation, pain, or redness persists or worsens

Stop use and ask a doctor if persistent or severe inflammatino occurs, which may indicate Iodine or Phenol sensitivity.

Keep out of reech of children.

If more than what remains in mouth after spitting out is accidentally swallowed, get medical help or contact a Poison Control Center right away.

Directions

- Adults and children 12 years of age and older: gargle or swish around the mouth for at least 15 seconds and then spit out. Use every 2 hours or as directed by a dentis or doctor.
- Children 6 to under 12 years of age: apply 10 milliliters to the affected area, gargle or swish around the mouth for at least 15 seconds then spit out. Use every 2 hours or as directed by a dentist or doctor. Children under 12 years of age should be supervised in the use of this product.
- Children under 6 years of age: consult a dentist or doctor

Other information

- store at 15o-30oC (59o-86oF)

Inactive ingredients

boric acid, carrageenan, chlorophyllin copper complex sodium, methyl salicylate, purified water, sodium chloride, sorbitol, strong iodine solution.

OTC - PURPOSE SECTION

Uses

- temporary relief of occasional minor irritation, pain, sore mouth, and sore throat.

OTC - KEEP OUT OF REACH OF CHILDREN SECTION

Keep out of reech of children.

If more than what remains in mouth after spitting out is accidentally swallowed, get medical help or contact a Poison Control Center right away.

INDICATIONS & USAGE SECTION

Other information

- store at 15o-30oC (59o-86oF)

WARNINGS SECTION

Warnings

If used for sore throat:

Consult a doctor promplty if sore throat is

- severe or persists more than 2 daysaccompanied by :
- rash
- swelling
- fever
- headache
- nausea
- vomiting

Unless directed by a doctor do not administer to children under 3 years of age.

If used for sore mouth:

See your dentist or doctor promptly if

- sore mouth symptoms do not improve in 7 days.
- irritation, pain, or redness persists or worsens

Stop use and ask a doctor if persistent or severe inflammatino occurs, which may indicate Iodine or Phenol sensitivity.

DOSAGE & ADMINISTRATION SECTION

Directions

- Adults and children 12 years of age and older: gargle or swish around the mouth for at least 15 seconds and then spit out. Use every 2 hours or as directed by a dentis or doctor.
- Children 6 to under 12 years of age: apply 10 milliliters to the affected area, gargle or swish around the mouth for at least 15 seconds then spit out. Use every 2 hours or as directed by a dentist or doctor. Children under 12 years of age should be supervised in the use of this product.Children under 6 years of age: consult a dentist or doctor
- Children under 6 years of age: consult a dentist or doctor

INACTIVE INGREDIENT SECTION

Inactive ingredients

boric acid, carrageenan, chlorophyllin copper complex sodium, methyl salicylate, purified water, sodium chloride, sorbitol, strong iodine solution.